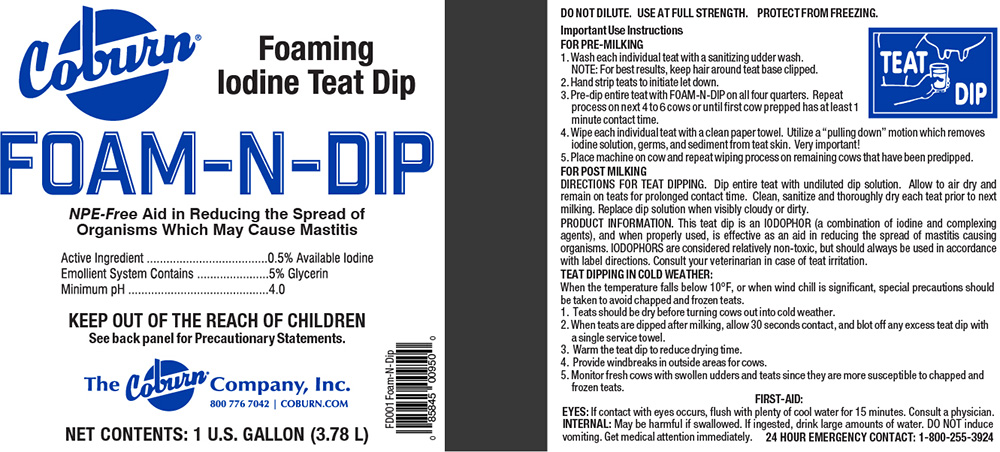 DRUG LABEL: Coburn FOAM-N-DIP
NDC: 60282-3106 | Form: LIQUID
Manufacturer: Stearns Packaging Corporation
Category: animal | Type: OTC ANIMAL DRUG LABEL
Date: 20251201

ACTIVE INGREDIENTS: IODINE 0.5 kg/100 L
INACTIVE INGREDIENTS: GLYCERIN 5 kg/100 L

Iodine Teat Dip

GENERAL PRECAUTIONS

IODOPHORS are considered relatively non-toxic, but should always
be used in accordance with label directions. Consult your veterinarian in case of teat irritation.

TEAT DIPPING IN COLD WEATHER:
When the temperature falls below 10 degrees F, or when wind chill is significant,
special precautions should be taken to avoid chapped and frozen teats.
1. Teats should be dry before turning cows out into cold weather.
2. When teats are dipped after milking, allow 30 seconds contact, and blot off any excess
teat dip with a single service towel.
3. Warm the teat dip to reduce drying time.
4. Provide windbreaks in outside areas for cows.
5. Monitor fresh cows with swollen udders and teats since they are more susceptible to
chapped and frozen teats.

DESCRIPTION

PRODUCT INFORMATION: This teat dip is an IODOPHOR (a combination of
iodine and complexing agents), and when properly used, is effective as an
aid in reducing the spread of mastitis causing organisms.

DOSAGE AND ADMINISTRATION

DO NOT DILUTE. USE AT FULL STRENGTH. PROTECT FROM FREEZING.
Important Use Instructions
FOR PRE-MILKING
1. Wash each individual teat with a sanitizing udder wash.
NOTE: For best results, keep hair around teat based clipped.
2. Hand strip teats to initial let down.
3. Pre-dip entire teat with PRE-POST 1/2% on all four quarters. Repeat
process on next 4 to 6 cows or until first cow prepped has at least 1
minute contact time.
4. Wipe each individual teat with a clean paper towel. Utilize a "pulling down" motion which removes
iodine solution, germs, and sediment from teat skin. Very important!
5. Place machine on cow and repeat wiping process on remaining cows that have been predipped.
FOR POST MILKING
DIRECTIONS FOR TEAT DIPPING. Dip entire teat with undiluted dip solution. Allow to air dry and
remain on teats for prolonged contact time. Clean, sanitize and thoroughly dryeach teat prior to next milking. Replace dip solution when visibly cloudy or dirty.

USER SAFETY WARNINGS

FIRST-AID:
EYES: If contact with eyes occurs, flush with plenty of cool water for 15 minutes. Consult a physician.
INTERNAL: May be harmful if swallowed. If ingested, drink large amounts of water. DO NOT induce
vomiting. Get medical attention immediately. 24 HOUR EMERGENCY CONTACT: 1-800-255-3924

PACKAGE LABEL

Coburn Foaming
Iodine Teat Dip

FOAM-N-DIP

NPE-Free Aid in Reducing the Spread of
Organisms Which May Cause Mastitis

Active Ingredient...........................0.5% Available Iodine
Emollient System Contains............5% Glycerin
Minimum pH...................................4.0

KEEP OUT OF THE REACH OF CHILDREN
See back panel for Precautionary Statements

The Coburn Company, Inc.
800 776 7024 | COBURN.COM

NET CONTENTS: 1 U.S. GALLON (3.78 L)